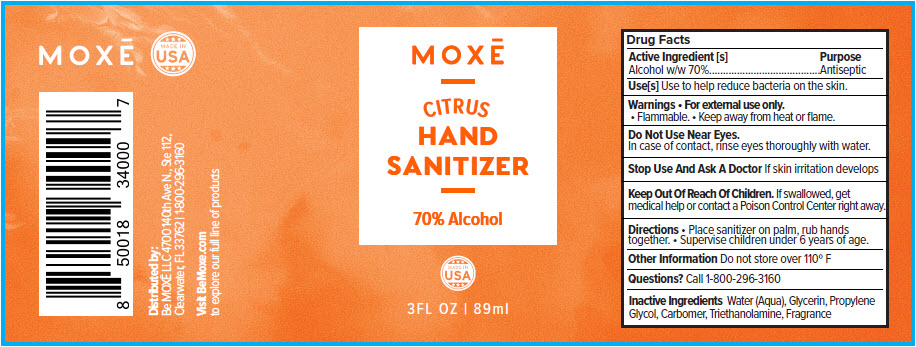 DRUG LABEL: MOXE CITRUS HAND SANITIZER
NDC: 75435-003 | Form: GEL
Manufacturer: Be Moxe, LLC
Category: otc | Type: HUMAN OTC DRUG LABEL
Date: 20200813

ACTIVE INGREDIENTS: Alcohol 70 mL/100 mL
INACTIVE INGREDIENTS: Water; Glycerin; Propylene Glycol; Carbomer Homopolymer, Unspecified Type; Trolamine

MOXĒ CITRUS HAND SANITIZER

Drug Facts

Active Ingredient [s]

Alcohol w/w 70%

Purpose

Antiseptic

Use[s]

Use to help reduce bacteria on the skin.

Warnings

- For external use only.
- Flammable.
- Keep away from heat or flame.

Do Not Use Near Eyes.

In case of contact, rinse eyes thoroughly with water.

Stop Use And Ask A Doctor

If skin irritation develops

Keep Out Of Reach Of Children. If swallowed, get medical help or contact a Poison Control Center right away.

Directions

- Place sanitizer on palm, rub hands together.
- Supervise children under 6 years of age.

Other Information

Do not store over 110° F

Questions?

Call 1-800-296-3160

Inactive Ingredients

Water (Aqua), Glycerin, Propylene Glycol, Carbomer, Triethanolamine, Fragrance

Distributed by:
Be MOXĒ LLC 4700 140th Ave N., Ste 112,
Clearwater, FL 33762

PRINCIPAL DISPLAY PANEL - 89 ml Bottle Label

MOXĒ

CITRUS
HAND
SANITIZER

70% Alcohol

MADE IN
USA

3FL OZ | 89ml